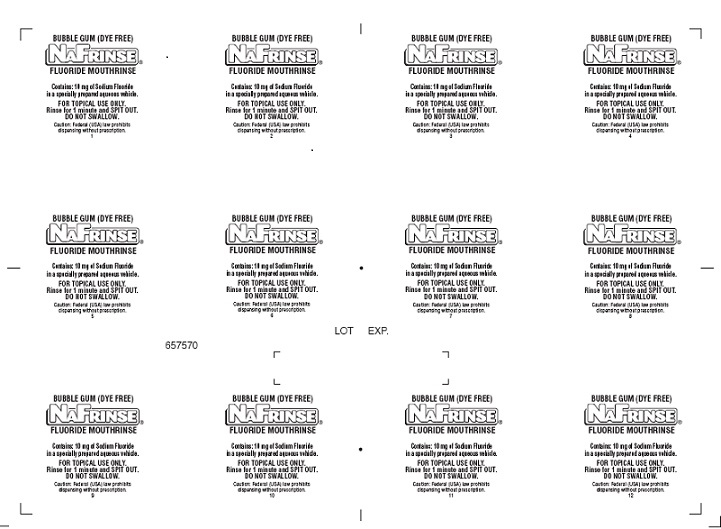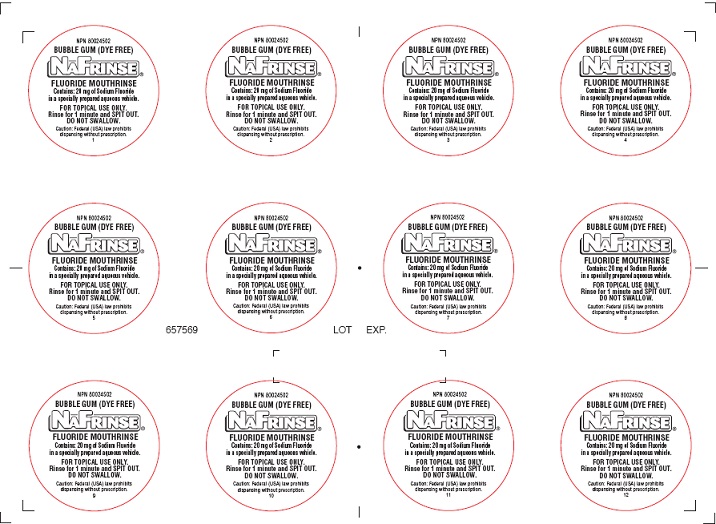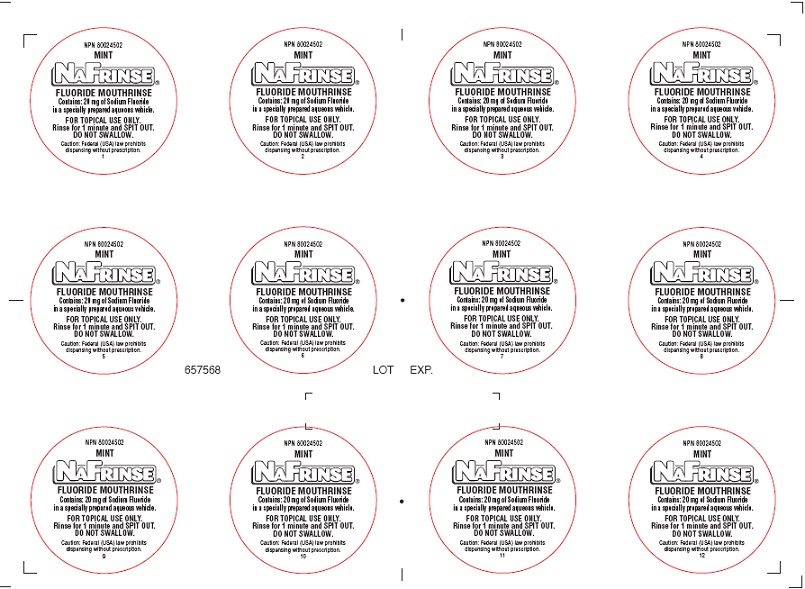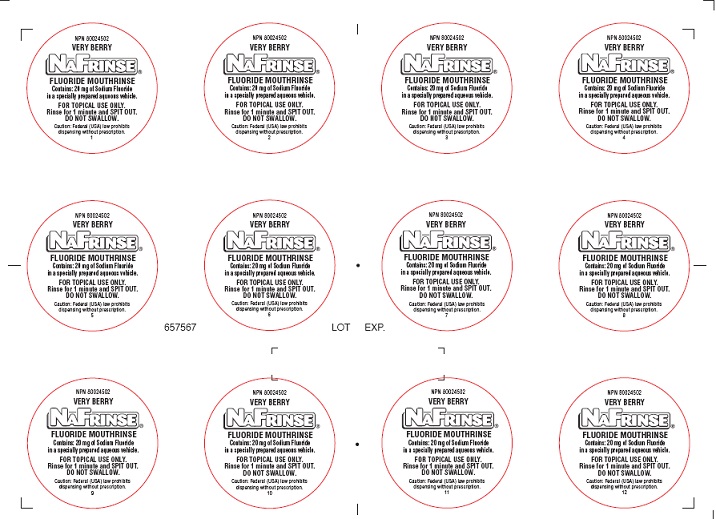 DRUG LABEL: NAFRINSE UNIT DOSE MINT FLAVOR
NDC: 0273-8002 | Form: SOLUTION
Manufacturer: Young Dental Manufacturing Co 1, LLC.
Category: prescription | Type: HUMAN PRESCRIPTION DRUG LABEL
Date: 20181214

ACTIVE INGREDIENTS: Sodium Fluoride 2 mg/1 mL
INACTIVE INGREDIENTS: SACCHARIN SODIUM; Potassium Sorbate; ANHYDROUS CITRIC ACID

Active Ingredients

Sodium Fluoride

Inactives

Saccharin Sodium, Potassium Sorbate, Citric Acid, Flavoring

Dye (Only present in Mint and Very Berry flavors)

Purpose

Prevention of dental caries.

Warning:

a) Do not swallow b) Do not eat, drink or rinse with water for 30 minutes after use. c) Instruct children under 12 years of age in the use of the product and in good brushing and rinsing habits to minimize swallowing d) Not recommended for use in children younger than 6 years of age.

Dosage and Administration:

DIRECTIONS FOR USE: {Best Results • Use Early Morning)

1. Each pupil receives one cup and one napkin. 2. Have the pupils remove the lids from the cups. 3. Have the pupils empty the contents of the cup into their mouths and swish thoroughly for one minute. 4. HOLD CUP AGAINST THE MOUTH. Spit solution back into the cup. 5. Have the pupils wipe their mouths with the napkin; then stuff the napkin slowly into the cup to absorb the solution. 6. Discard the cup with the napkin into the provided trash bag. a) Do not swallow b) Do not eat, drink or rinse with water for 30 minutes after use. c) Instruct children under 12 years of age in the use of the product and in good brushing and rinsing habits to minimize swallowing d) Not recommended for use in children younger than 6 years of age. ADDITIONAL INSTRUCTIONS/IMPORTANT: In order to avoid spillage of the solution from the cup, the children must be instructed to do the following: 1) When spitting the fluoride solution from the mouth back into the cup, the children must hold the cup close to the mouth, and spit slowly into the cup. 2) The napkins must be stuffed into the cups very slowly in order to avoid spillage.

Keep out of reach of children